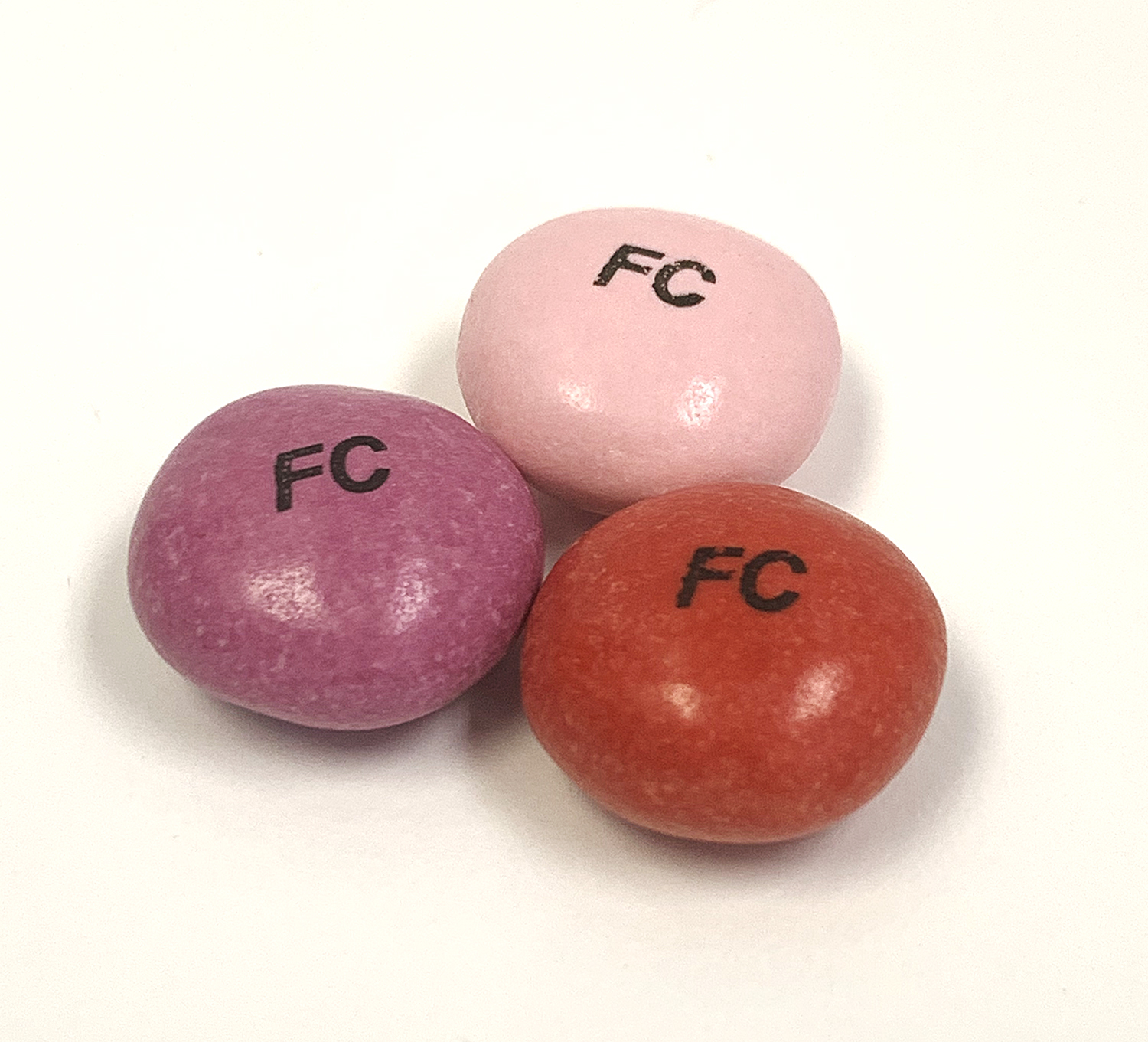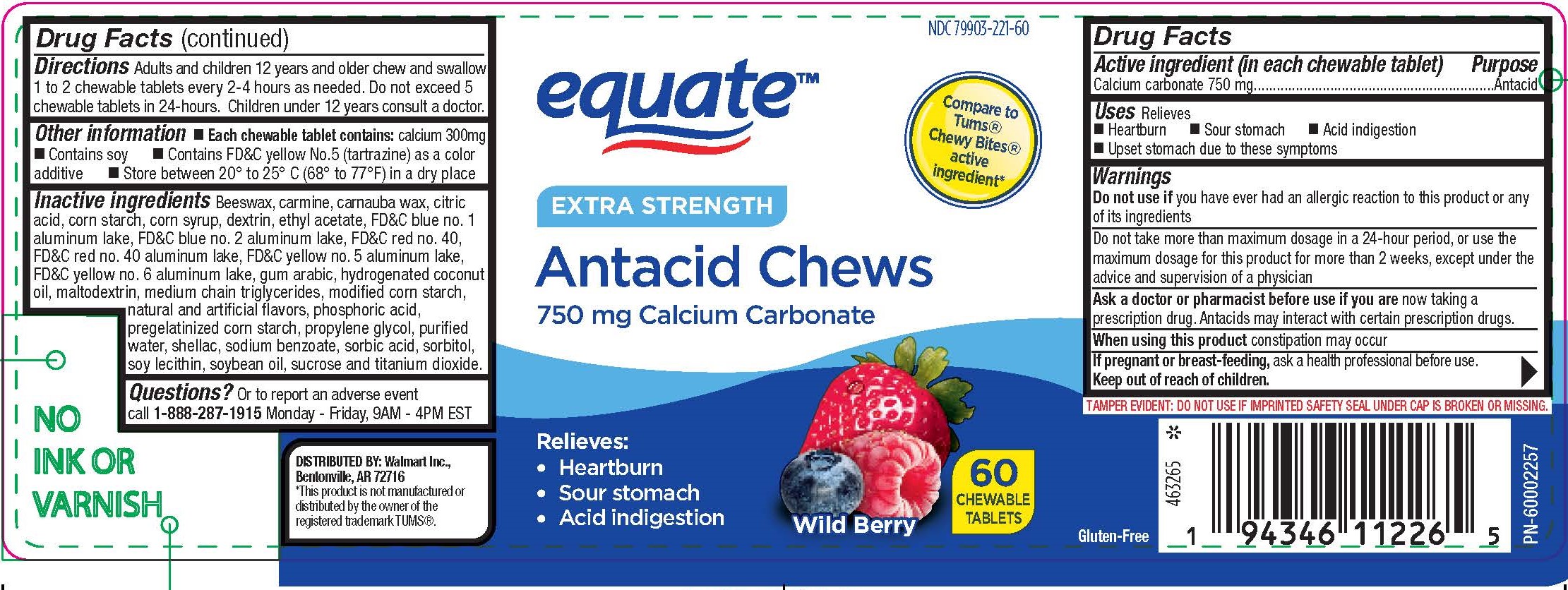 DRUG LABEL: Equate Wild Berry Antacid Chews
NDC: 79903-221 | Form: TABLET, CHEWABLE
Manufacturer: Walmart
Category: otc | Type: HUMAN OTC DRUG LABEL
Date: 20251223

ACTIVE INGREDIENTS: CALCIUM CARBONATE 750 mg/1 1
INACTIVE INGREDIENTS: SUCROSE

Calcium Carbonate 750 mg

Active ingredient (in each chewable tablet)

Calcium Carbonate 750 mg

Purpose

Antacid

INDICATIONS AND USAGE

Uses Relieves

- Heartburn
- Sour stomach
- Acid indigestion
- Upset stomach due to these symptoms

Warnings

Do not use if you have ever had an allergic reaction to this product or any of its ingredients.

Do not take more than maximum dosage in a 24-hour perios, or use the maximum dosage for this product for more than 2 weeks, except under the advice and supervision of a physician.

Ask a doctor or pharmacist before use if you are now taking a prescription drug. Antacids may interact with certain prescription drugs.

When using this product constipation may occur

PREGNANCY OR BREAST FEEDING

If pregnant or breast-feeding, ask a health professional before use.

Keep out of reach of children.

DOSAGE AND ADMINISTRATION

Directions: Adults and children 12 years and older chew and swallow 1 to 2 chewable tablets every 2 - 4 hours as needed. Do not exceed 5 chewable tablets in 24-hours. Children under 12 years consult a doctor.

Other information

- Each chewable tablet contains: calcium 300mg
- Contains soy
- Contains FD&C yellow No. 5 (tartrazine) as a color additive
- Store between 20° to 25°C (68° to 77°F) in a dry place

INACTIVE INGREDIENT

Inactive ingredients: Beeswax, carmine, carnauba wax, citric acid, corn starch, corn syrup, dextrin, ethyl acetate, FD&C blue no. 1 aluminum lake, FD&C blue no. 2 aluminum lake, FD&C red no. 40, FD&C red no. 40 aluminum lake, FD&C yellow no. 5 aluminum lake, FD&C yellow no. 6 aluminum lake, gum arabic, hydrogenated cocomut oil, maltodextrin, medium chain triglycerides, modified corn starch, natural and artificial flavors, phosphoric acid, pregenatinized corn starch, propylene glycol, purified water, shellac, sodium benzoate, sorbic acid, sorbitol, soy lecithin, soybean oil, sucrose and titanium dioxide.

QUESTIONS

Questions? Or to report an adverse event call 1-888-287-1915. Monday - Friday, 9AM to 4PM EST